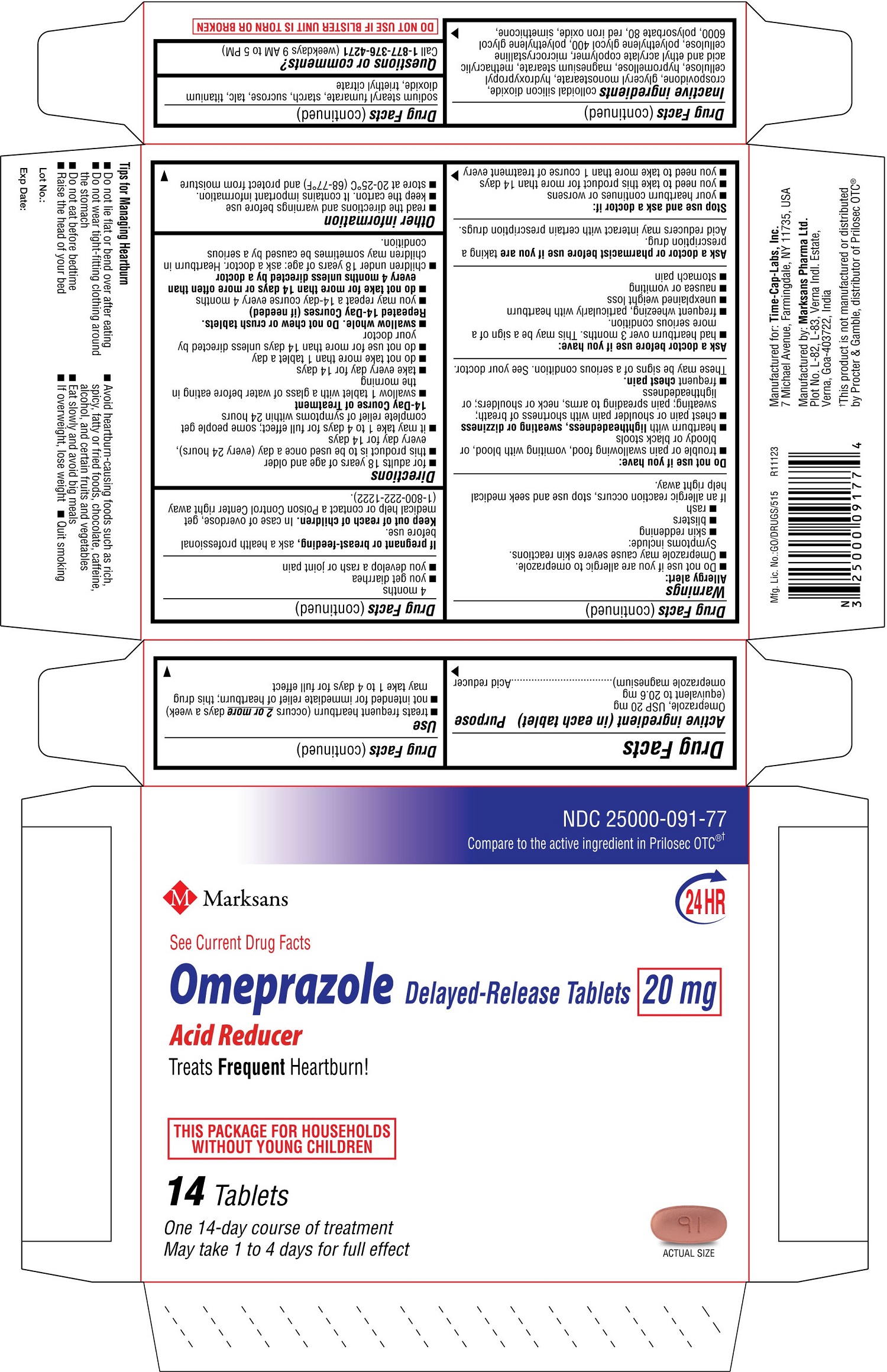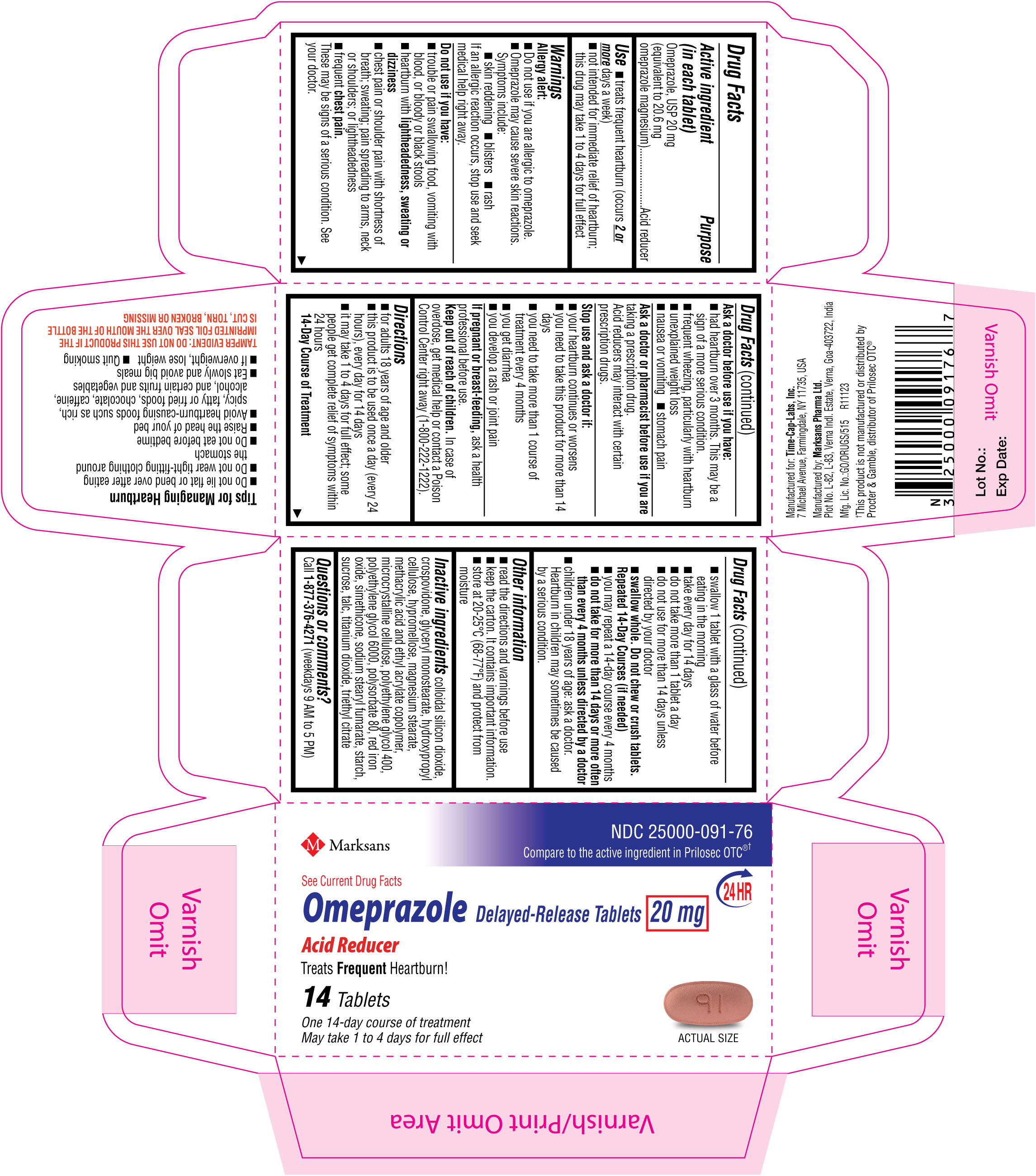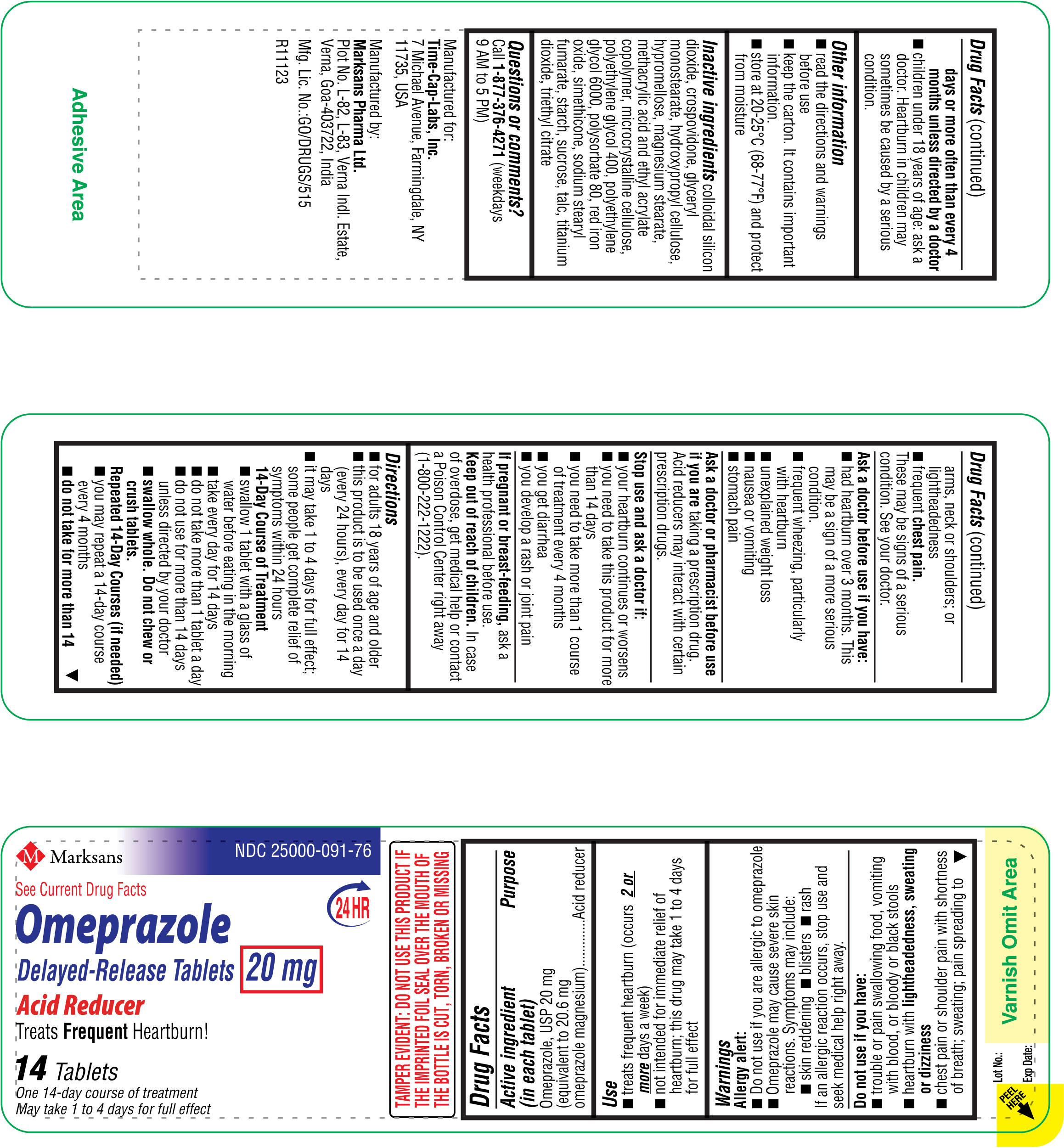 DRUG LABEL: Omeprazole 20 mg
NDC: 25000-091 | Form: TABLET, DELAYED RELEASE
Manufacturer: MARKSANS PHARMA LIMITED
Category: otc | Type: Human OTC Drug Label
Date: 20250811

ACTIVE INGREDIENTS: OMEPRAZOLE MAGNESIUM 20 mg/1 1
INACTIVE INGREDIENTS: GLYCERYL MONOSTEARATE; SILICON DIOXIDE; CROSPOVIDONE, UNSPECIFIED; HYDROXYPROPYL CELLULOSE, UNSPECIFIED; HYPROMELLOSE, UNSPECIFIED; MAGNESIUM STEARATE; METHACRYLIC ACID AND ETHYL ACRYLATE COPOLYMER; MICROCRYSTALLINE CELLULOSE; POLYETHYLENE GLYCOL 400; POLYETHYLENE GLYCOL 6000; POLYSORBATE 80; FERRIC OXIDE RED; DIMETHICONE; SODIUM STEARYL FUMARATE; STARCH, CORN; SUCROSE; TALC; TITANIUM DIOXIDE; TRIETHYL CITRATE

Omeprazole Delayed Release Tablets 20 mg

ACTIVE INGREDIENT(S)

Active ingredient (in each tablet)
Omeprazole, USP 20 mg
(equivalent to 20.6 mg omeprazole magnesium)

PURPOSE

Acid reducer

USE(S)

Uses
• treats frequent heartburn (occurs 2 or more days a week)
• not intended for immediate relief of heartburn; this drug may take 1 to 4 days for full effect

WARNINGS

Allergy alert:

- Do not use if you are allergic to Omeprazole

- Omeprazole may cause severe skin reactions. Symptoms include:
  - skin reddening
  - blisters
  - rash
  If an allergic reaction occurs, stop use and seek medical attention right away.

Do not use if you have:
• trouble or pain swallowing food, vomiting with blood, or bloody or black stools
• heartburn with lightheadedness, sweating or dizziness
• chest pain or shoulder pain with shortness of breath; sweating; pain spreading to arms, neck or shoulders; or lightheadedness
• frequent chest pain
These may be signs of a serious condition. See your doctor.

Ask a doctor before use if you have:
• had heartburn over 3 months. This may be a sign of a more serious condition.
• frequent wheezing, particularly with heartburn
• unexplained weight loss
• nausea or vomiting
• stomach pain

Ask a doctor or pharmacist before use if you are taking a prescription drug.
Acid reducers may interact with certain prescription drugs.

STOP USE AND ASK DOCTOR IF

Stop use and ask a doctor if
• your heartburn continues or worsens
• you need to take this product for more than 14 days
• you need to take more than 1 course of treatment every 4 months
• you get diarrhea
• you develop a rash or joint pain

PREGNANCY/BREASTFEEDING

If pregnant or breast-feeding, ask a health professional before use.

Keep out of reach of children. In case of overdose, get medical help or contact a Poison Control Center right away (1-800-222-1222).

DIRECTIONS

- for adults 18 years of age and older
- this product is to be used once a day (every 24 hours), every day for 14 days
- it may take 1 to 4 days for full effect; some people get complete relief of symptoms within 24 hours

14-Day Course of Treatment

- swallow 1 tablet with a glass of water before eating in the morning
- take every day for 14 days
- do not take more than 1 tablet a day
- do not use for more than 14 days unless directed by your doctor
- swallow whole. Do not chew or crush tablets.

Repeated 14-Day Courses (if needed)

- you may repeat a 14-day course every 4 months
- do not take for more than 14 days or more often than every 4 months unless directed by a doctor

- children under 18 years of age: ask a doctor. Heartburn in children may sometimes be caused by a serious condition.

STORAGE

Other information

- read the directions and warnings before use
- keep the carton. It contains important information.
- store at 20-25°C (68-77°F) and protect from moisture

INACTIVE INGREDIENTS

colloidal silicone dioxide, crospovidone, glyceryl monostearate, hydroxypropyl cellulose, hypromellose, magnesium stearate, methacrylic acid and ethyl acrylate copolymer, microcrystalline cellulose, polyethylene glycol 400, polyethylene glycol 6000, polysorbate 80, red iron oxide, simethicone, sodium stearyl fumarate, starch, sucrose, talc, titanium dioxide, triethyl citrate

Questions or comments? Call 1-877-376-4271 (weekdays 9 AM to 5 PM)
Tips for Managing Heartburn
• Do not lie flat or bend over after eating.
• Do not wear tight-fitting clothing around the stomach.
• Do not eat before bedtime.
• Raise the head of your bed.
• Avoid heartburn-causing foods such as rich, spicy, fatty or fried foods, chocolate, caffeine, alcohol and certain fruits and vegetables.
• Eat slowly and do not eat big meals.
• If overweight, lose weight.
• Quit smoking.
Manufactured for:
Time-Cap Labs, Inc.
7 Michael Avenue,
Farmingdale,
NY 11735, USA
Manufactured by:
Marksans Pharma Ltd.
Plot No. L-82, L-83
Verna Indl. Estate
Verna, Goa-403722, India

PRINCIPAL DISPLAY PANEL

NDC: 25000-091-76
Omeprazole Delayed-Release Tablets 20 mg
14's count Carton

NDC: 25000-091-76
Omeprazole Delayed-Release Tablets 20 mg
14's count Label

NDC: 25000-091-77
Omeprazole Delayed-Release Tablets 20 mg
14's count (2 x 7's blister) Carton